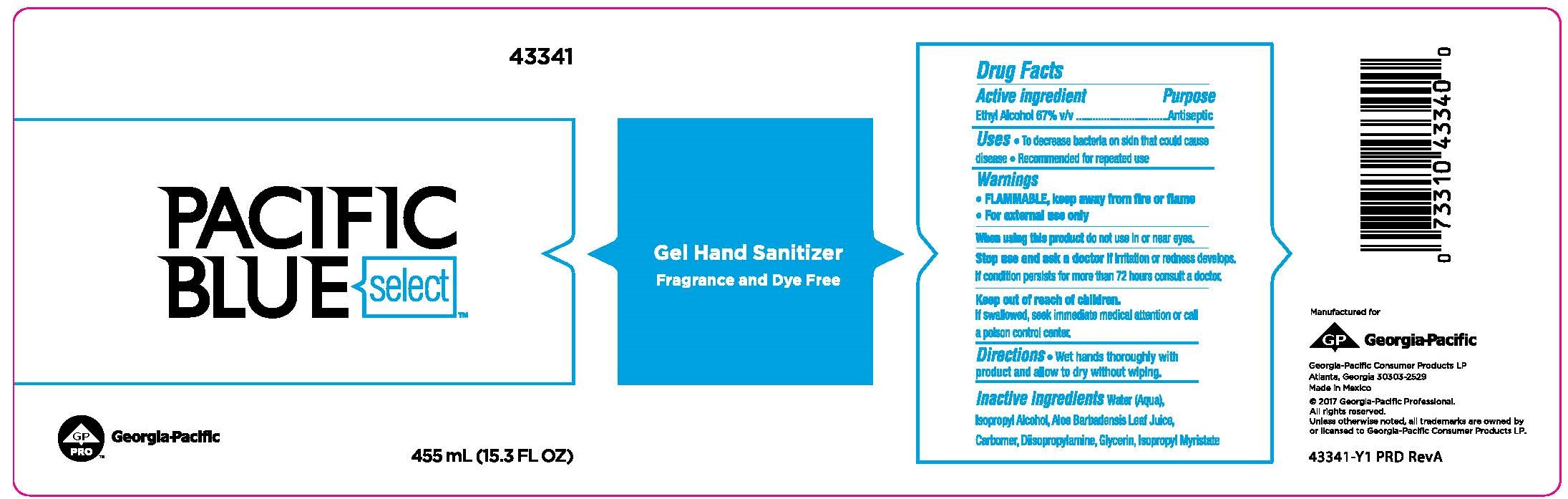 DRUG LABEL: Pacific Blue Select Gel Hand Sanitizer Fragrance and Dye Free
NDC: 54622-308 | Form: LIQUID
Manufacturer: Georgia-Pacific Consumer Products
Category: otc | Type: HUMAN OTC DRUG LABEL
Date: 20240502

ACTIVE INGREDIENTS: ALCOHOL 67 mL/100 mL
INACTIVE INGREDIENTS: WATER; ISOPROPYL ALCOHOL; ALOE VERA LEAF; SODIUM BENZOATE; ANHYDROUS CITRIC ACID; POTASSIUM SORBATE; SODIUM SULFITE; CARBOMER INTERPOLYMER TYPE A (ALLYL SUCROSE CROSSLINKED); DIISOPROPYLAMINE; GLYCERIN; ISOPROPYL MYRISTATE

54622-308

Drug Facts

Active ingredient

Ethyl alcohol, 67% v/v

Purpose

Antiseptic

Uses

- To decrease bacteria on skin that could cause disease
- Recommended for repeated use

Warnings

- FLAMMABLE, keep away from fire or flame
- For external use only

When using this product

Do not use in or near eyes.

Stop use and ask a doctor

if irritation or redness develops. If condition persists for more than 72 hours consult a doctor.

Keep out of reach of children.

If swallowed, seek immediate medical attention or call a poison control center.

Directions

Wet hands thoroughly with product and allow to dry without wiping.

Inactive ingredients

Water (Aqua), Isopropyl Alcohol, Aloe Barbadensis Leaf Juice, Carbomer, Diisopropylamine, Glycerin, Isopropyl Myristate.

PACKAGE LABEL

Pacific Blue Select™
Gel Hand Sanitizer
Fragrance and Dye Free
455mL (15.3 FL OZ)
Georgia-Pacific Consumer Products LP
Atlanta, GA 30303-2529
Made in Mexico
©2017 Georgia-Pacific Professional.
All rights reserved.
Unless otherwise noted, all trademarks are owned by
or licensed to Georgia-Pacific Consumer Products LP.